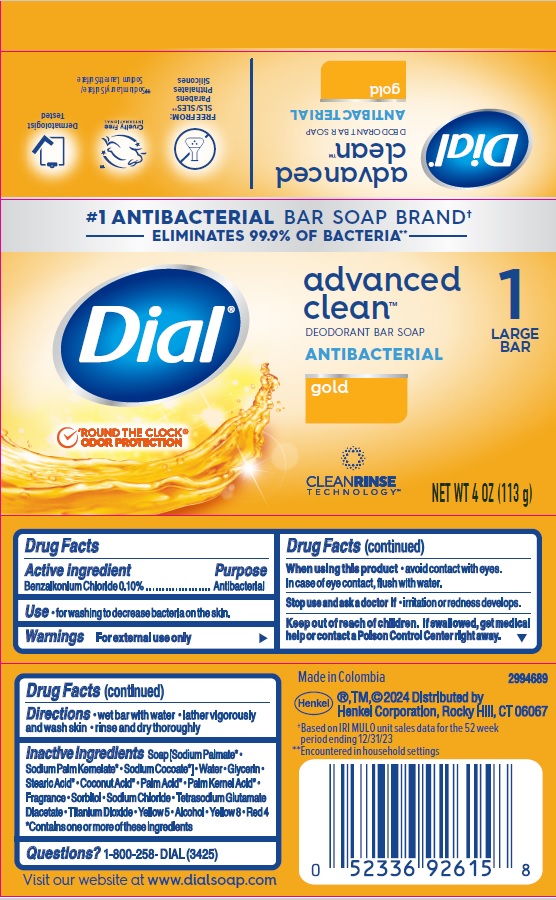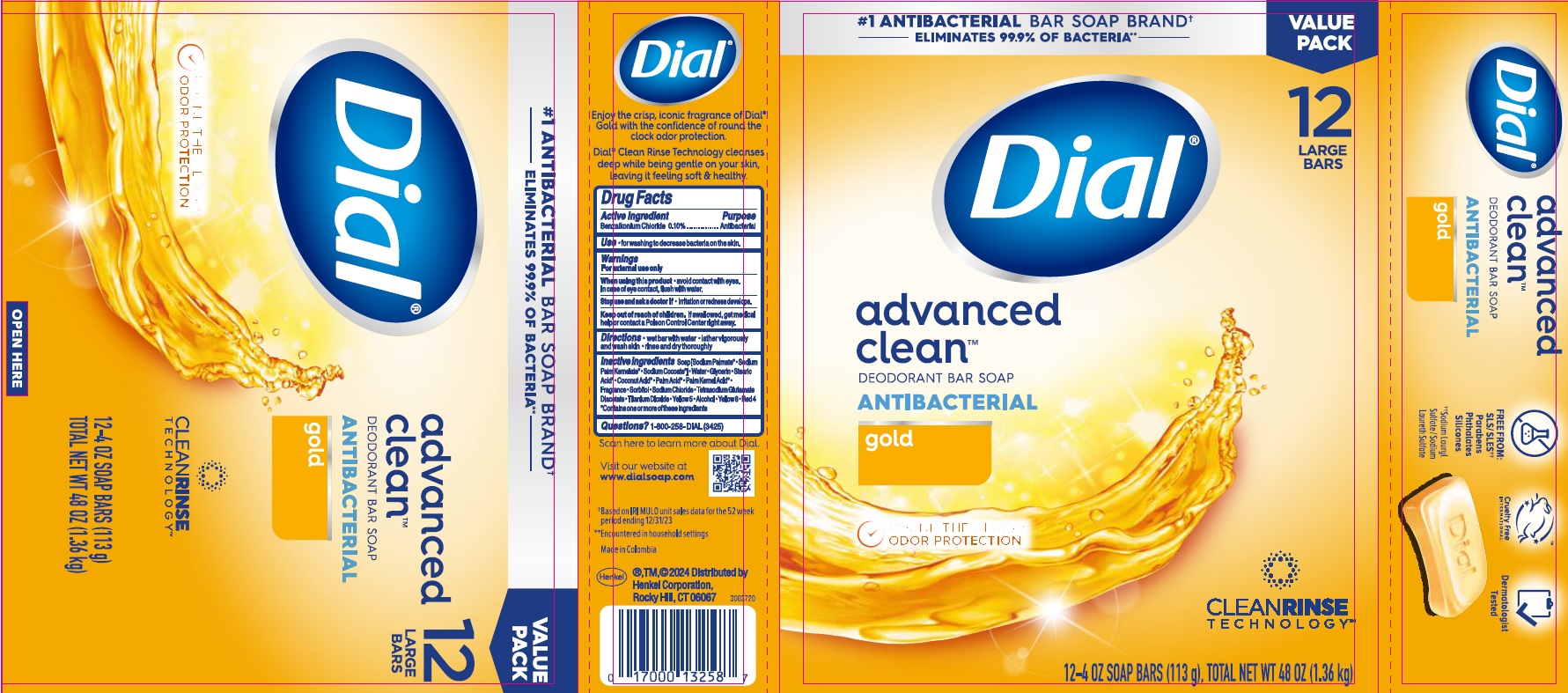 DRUG LABEL: Dial advanced clean
NDC: 54340-262 | Form: SOAP
Manufacturer: Henkel Corporation
Category: otc | Type: HUMAN OTC DRUG LABEL
Date: 20241111

ACTIVE INGREDIENTS: BENZALKONIUM CHLORIDE 0.1 g/100 g
INACTIVE INGREDIENTS: FD&C RED NO. 4; FD&C YELLOW NO. 5; SODIUM PALMATE; SODIUM COCOATE; COCONUT ACID; STEARIC ACID; SORBITOL; TETRASODIUM GLUTAMATE DIACETATE; PALM ACID; GLYCERIN; WATER; PALM KERNEL ACID; ALCOHOL; TITANIUM DIOXIDE; SODIUM CHLORIDE; SODIUM PALM KERNELATE; FLUORESCEIN SODIUM

Dial advanced clean deodorant bar soap Antibacterial gold

Drug Facts

Active ingredient

Benzalkonium Chloride 0.1%

Purpose

Antibacterial

INDICATIONS AND USAGE

UseFor washing to decrease bacteria on the skin.

Warnings

For external use only

WHEN USING

When using this productavoid contact with eyes. In case of eye contact, flush with water.

Stop use and ask a doctor ifirritation and redness develops.

Keep out of reach of children. If swallowed, get medical help or contact a Poison Control Center right away.

DOSAGE AND ADMINISTRATION

Directions • wet bar with water • Lather vigorously and wash skin • Rinse and dry thoroughly

INACTIVE INGREDIENT

Inactive ingredientsSoap [Sodium Palmate* • Sodium Palm Kernelate*• Sodium Cocoate*] • Water • Glycerin • Stearic Acid* • Coconut Acid* • Palm Acid* • Palm Kernel Acid* • Fragrance • Sorbitol • Sodium Chloride • Tetrasodium Glutamate Diacetate •Titanium Dioxide • Yellow 5 • Alcohol • Yellow 8 • Red 4

*Contains one or more of these ingredients

Questions?1-800-258-DIAL (3425)

Visit our website at www.dialsoap.com

Made in Columbia

Henkel®, TM, ©2024 Distributed by

Henkel Corporation, Rocky Hill, CT 06067

PACKAGE LABEL

ELIMINATES 99% OF BACTERIA**

Dial®advanced clean™

DEODORANT BAR SOAP

ANTIBACTERIAL

gold

NET WT 4 OZ (113 g)